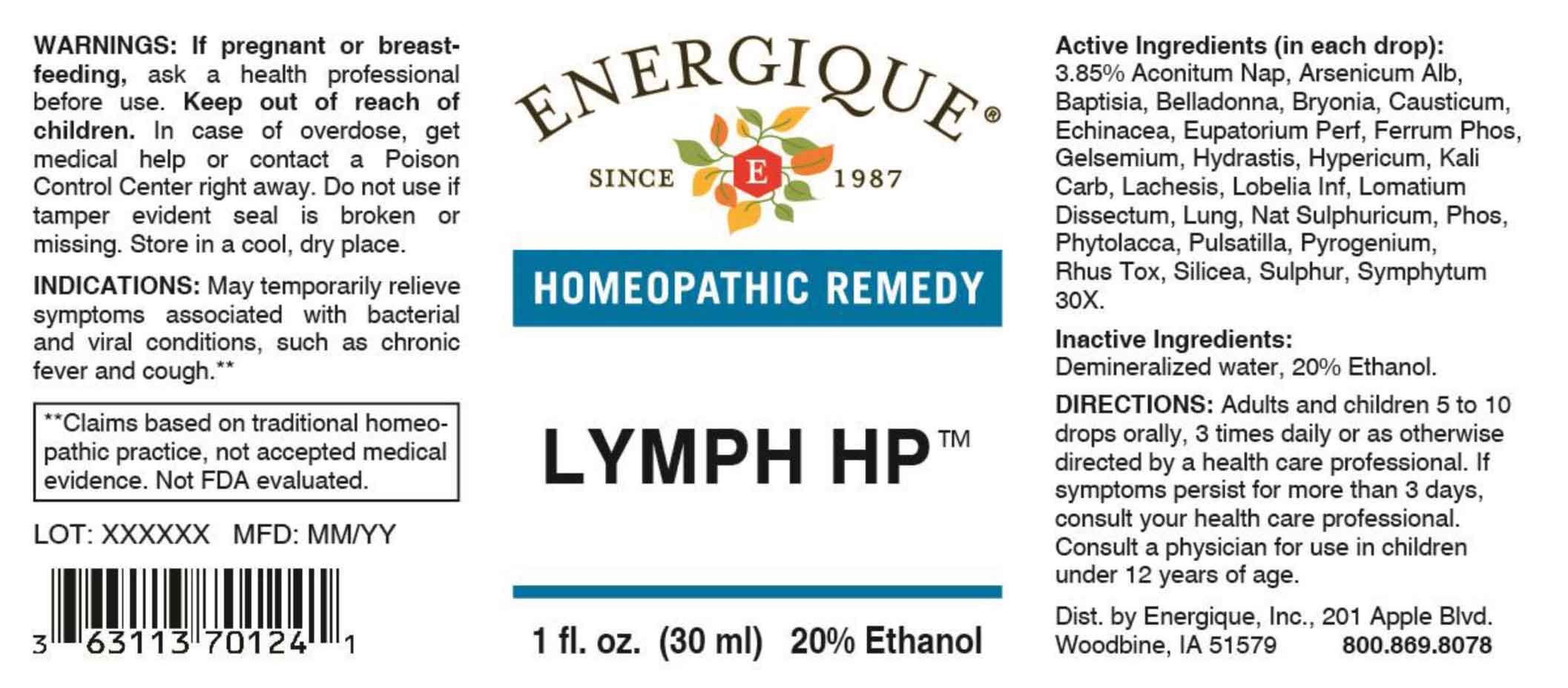 DRUG LABEL: Lymph HP
NDC: 44911-0616 | Form: LIQUID
Manufacturer: Energique, Inc.
Category: homeopathic | Type: HUMAN OTC DRUG LABEL
Date: 20251124

ACTIVE INGREDIENTS: ACONITUM NAPELLUS WHOLE 30 [hp_X]/1 mL; ARSENIC TRIOXIDE 30 [hp_X]/1 mL; BAPTISIA TINCTORIA ROOT 30 [hp_X]/1 mL; ATROPA BELLADONNA WHOLE 30 [hp_X]/1 mL; BRYONIA ALBA ROOT 30 [hp_X]/1 mL; CAUSTICUM 30 [hp_X]/1 mL; ECHINACEA ANGUSTIFOLIA WHOLE 30 [hp_X]/1 mL; EUPATORIUM PERFOLIATUM FLOWERING TOP 30 [hp_X]/1 mL; FERROSOFERRIC PHOSPHATE 30 [hp_X]/1 mL; GELSEMIUM SEMPERVIRENS ROOT 30 [hp_X]/1 mL; GOLDENSEAL 30 [hp_X]/1 mL; HYPERICUM PERFORATUM 30 [hp_X]/1 mL; POTASSIUM CARBONATE 30 [hp_X]/1 mL; LACHESIS MUTA VENOM 30 [hp_X]/1 mL; LOBELIA INFLATA WHOLE 30 [hp_X]/1 mL; LOMATIUM DISSECTUM ROOT 30 [hp_X]/1 mL; SUS SCROFA LUNG 30 [hp_X]/1 mL; SODIUM SULFATE 30 [hp_X]/1 mL; PHOSPHORUS 30 [hp_X]/1 mL; PHYTOLACCA AMERICANA ROOT 30 [hp_X]/1 mL; PULSATILLA VULGARIS WHOLE 30 [hp_X]/1 mL; RANCID BEEF 30 [hp_X]/1 mL; TOXICODENDRON PUBESCENS LEAF 30 [hp_X]/1 mL; SILICON DIOXIDE 30 [hp_X]/1 mL; SULFUR 30 [hp_X]/1 mL; COMFREY ROOT 30 [hp_X]/1 mL
INACTIVE INGREDIENTS: WATER; ALCOHOL

DRUG FACTS:

ACTIVE INGREDIENTS:

(in each drop): 3.85% Aconitum Napellus 30X, Arsenicum Album 30X, Baptisia Tinctoria 30X, Belladonna 30X, Bryonia 30X, Causticum 30X, Echinacea 30X, Eupatorium Perfoliatum 30X, Ferrum Phosphoricum 30X, Gelsemium Sempervirens 30X, Hydrastis Canadensis 30X, Hypericum Perforatum 30X, Kali Carbonicum 30X, Lachesis Mutus 30X, Lobelia Inflata 30X, Lomatium Dissectum 30X, Lung 30X, Natrum Sulphuricum 30X, Phosphorus 30X, Phytolacca Decandra 30X, Pulsatilla 30X, Pyrogenium 30X, Rhus Tox 30X, Silicea 30X, Sulphur 30X, Symphytum Officinale 30X.

INDICATIONS:

May temporarily relieve symptoms associated with bacterial and viral conditions, such as chronic fever and cough.**

**Claims based on traditional homeopathic practice, not accepted medical evidence. Not FDA evaluated.

WARNINGS:

If pregnant or breast-feeding, ask a health professional before use.

Keep out of reach of children. In case of overdose, get medical help or contact a Poison Control Center right away.

Do not use if tamper evident seal is broken or missing. Store in a cool, dry place.

DIRECTIONS:

Adults and children 5 to 10 drops orally, 3 times daily or as otherwise directed by a health care professional. If symptoms persist for more than 3 days, consult your health care professional. Consult a physician for use in children under 12 years of age.

INACTIVE:

May temporarily relieve symptoms associated with bacterial and viral conditions, such as chronic fever and cough.**

**Claims based on traditional homeopathic practice, not accepted medical evidence. Not FDA evaluated.

INACTIVE INGREDIENTS:

Demineralized water, 20% Ethanol.

KEEP OUT OF REACH OF CHILDREN:

In case of overdose, get medical help or contact a Poison Control Center right away.

QUESTIONS:

Dist. by Energique, Inc.

201 Apple Blvd

Woodbine, IA 51579

800-869-8078

PACKAGE LABEL DISPLAY:

ENERGIQUE

SINCE 1987

HOMEOPATHIC REMEDY

LYMPH HP

1 fl. oz. (30 ml)